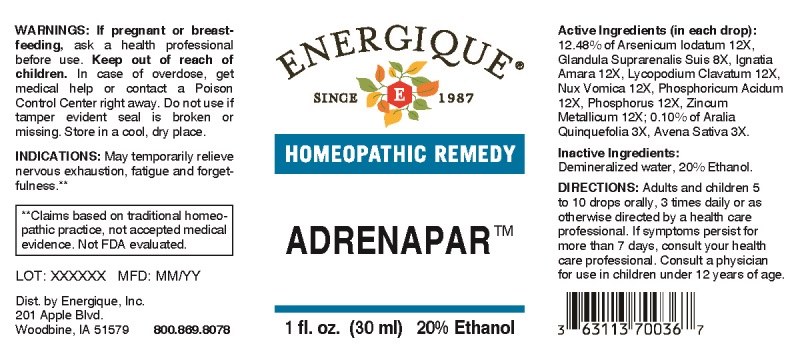 DRUG LABEL: Adrenapar
NDC: 44911-0476 | Form: LIQUID
Manufacturer: Energique, Inc.
Category: homeopathic | Type: HUMAN OTC DRUG LABEL
Date: 20240729

ACTIVE INGREDIENTS: AMERICAN GINSENG 3 [hp_X]/1 mL; AVENA SATIVA FLOWERING TOP 3 [hp_X]/1 mL; SUS SCROFA ADRENAL GLAND 8 [hp_X]/1 mL; ARSENIC TRIIODIDE 12 [hp_X]/1 mL; STRYCHNOS IGNATII SEED 12 [hp_X]/1 mL; LYCOPODIUM CLAVATUM SPORE 12 [hp_X]/1 mL; STRYCHNOS NUX-VOMICA SEED 12 [hp_X]/1 mL; PHOSPHORIC ACID 12 [hp_X]/1 mL; PHOSPHORUS 12 [hp_X]/1 mL; ZINC 12 [hp_X]/1 mL
INACTIVE INGREDIENTS: WATER; ALCOHOL

Drug Facts:

ACTIVE INGREDIENTS:

(in each drop): 12.48% of Arsenicum Iodatum 12X, Glandula Suprarenalis Suis 8X, Ignatia Amara 12X, Lycopodium Clavatum 12X, Nux Vomica 12X, Phosphoricum Acidum 12X, Phosphorus 12X, Zincum Metallicum 12X; 0.10% of Aralia Quinquefolia 3X, Avena Sativa 3X.

INDICATIONS:

May temporarily relieve nervous exhaustion, fatigue and forgetfulness.**

**Claims based on traditional homeopathic practice, not accepted medical evidence. Not FDA evaluated.

WARNINGS:

If pregnant or breastfeeding, ask a health professional before use.

Keep out of reach of children. In case of overdose, get medical help or contact a Poison Control Center right away.

Do not use if tamper evident seal is broken or missing.

Store in a cool, dry place.

Keep out of reach of children. In case of overdose, get medical help or contact a Poison Control Center right away.

DIRECTIONS:

Adults and children 5 to 10 drops orally, 3 times daily or as otherwise directed by a health care professional. If symptoms persist for more than 7 days, consult your health care professional. Consult a physician for use in children under 12 years of age.

INDICATIONS:

May temporarily relieve nervous exhaustion, fatigue and forgetfulness.**

**Claims based on traditional homeopathic practice, not accepted medical evidence. Not FDA evaluated.

INACTIVE INGREDIENTS:

Demineralized water, 20% Ethanol.

QUESTIONS:

Dist. by Energique, Inc.

201 Apple Blvd

Woodbine, IA 51579 800.869.8078

PACKAGE LABEL DISPLAY:

ENERGIQUE

SINCE 1987

HOMEOPATHIC REMEDY

ADRENAPAR

1 fl. oz. (30 ml)